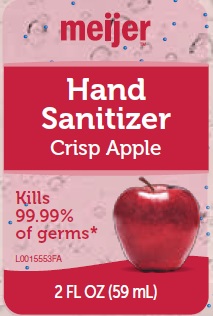 DRUG LABEL: Crisp Apple Hand Sani
NDC: 41250-607 | Form: LIQUID
Manufacturer: Meijer Distribution, Inc
Category: otc | Type: HUMAN OTC DRUG LABEL
Date: 20160311

ACTIVE INGREDIENTS: ALCOHOL 585 g/1 mL
INACTIVE INGREDIENTS: SULISOBENZONE; CARBOMER INTERPOLYMER TYPE A (ALLYL SUCROSE CROSSLINKED); POWDERED CELLULOSE; GLYCERIN; HYPROMELLOSES; MANNITOL; FD&C RED NO. 4; FD&C RED NO. 40; VITAMIN A PALMITATE; .ALPHA.-TOCOPHEROL ACETATE; ULTRAMARINE BLUE; WATER

Drug Facts

Active ingredient

Ethyl Alcohol 65%

Purpose

Antiseptic

Uses

- to decrease bacteria on the skin that could cause disease
- recommended for repeated use

Warnings

For external use only: hands

Flammable. Keep away from heat and flame

When using this product

- keep out of eyes. Incase of contact with eyes, flush thoroughly with water.
- do not inhale or ingest
- avoid contact with broken skin

Stop use and ask a doctor if

- irritation or redness develops
- condition persists for more than 72 hours

Keep out of reach of children.

If swallowed, get medical help or contact a Poison Control Center right away.

Directions

- wet hands thoroughly with product and allow to dry without wiping
- for children under 6, use only under adult supervision
- not recommed for infants

Other Information

- do not store above 105°F
- may discolor some fabrics
- harmful to wood finishes and plastics.

Inactive ingredients

benzophenone-4, carbomer, cellulose, fragrance, glycerin, hydroxypropyl methylcellulose, mannitol, red 4, red 40, retinyl palmitate, tocoperyl acetate, ultamarines, water

DISTRIBUTED BY MEIJER DISTRIBUTION, INC.

GRAND RAPIDS, MI 49544

www.meijer.com

Questions 1-888-593-0593

*Effective at eliminating 99.99% of many common harmful germs and bacteria in as little as 15 seconds

Principal Display Panel

Meijer

Hand Sanitizer

Crisp Apple

Kills 99.99% of germs*

2 FL OZ (59 mL)